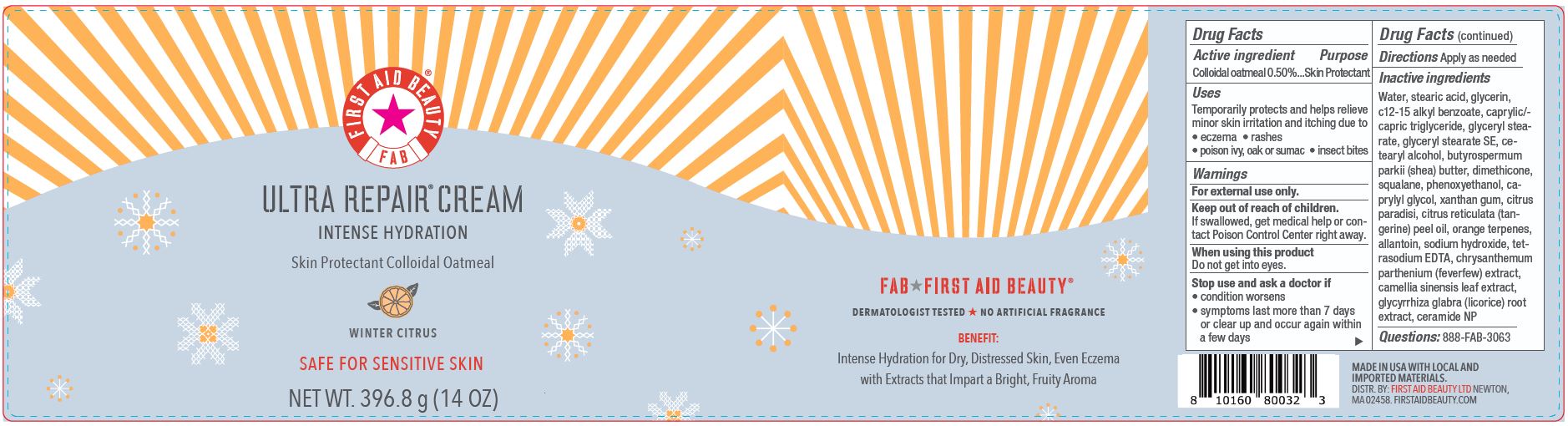 DRUG LABEL: First Aid Beauty FAB Ultra Repair Intense Hydration Skin Protectant Winter Citrus
NDC: 84126-049 | Form: CREAM
Manufacturer: The Procter & Gamble Manufacturing Company
Category: otc | Type: HUMAN OTC DRUG LABEL
Date: 20251218

ACTIVE INGREDIENTS: OATMEAL 0.5 g/100 g
INACTIVE INGREDIENTS: ORANGE TERPENES; GLYCERYL STEARATE SE; CETEARYL ALCOHOL; SQUALANE; DIMETHICONE; TETRASODIUM EDTA; C12-15 ALKYL BENZOATE; CAMELLIA SINENSIS LEAF; CAPRYLYL GLYCOL; SODIUM HYDROXIDE; PHENOXYETHANOL; BUTYROSPERMUM PARKII (SHEA) BUTTER; GLYCYRRHIZA GLABRA (LICORICE) ROOT; WATER; GLYCERIN; ALLANTOIN; GLYCERYL STEARATE; CAPRYLIC/CAPRIC TRIGLYCERIDE; STEARIC ACID; XANTHAN GUM; CERAMIDE NP; TANACETUM PARTHENIUM WHOLE; MANDARIN OIL; CITRUS PARADISI (GRAPEFRUIT) PEEL OIL

First Aid Beauty FAB Ultra Repair Cream Skin Protectant Winter Citrus

Drug Facts

Active ingredients

Colloidal Oatmeal 0.5%

Purpose

Skin Protectant

Uses

- Temporarily protects and helps relieve minor skin irritation and itching due to eczema, rashes, poison ivy, oak or sumac, insect bites

Warnings

For external use only.

Keep out of reach of children. If swallowed, get medical help or contact a Poison Control Center right away.

WHEN USING

Do not get into eyes.

Stop use and ask a doctor if condition worsens, symptoms last more than 7 days or clear up and occur again within a few days

Directions

Apply as needed

INACTIVE INGREDIENT

Water, stearic acid, glycerin, c12-15 alkyl benzoate, caprylic/- capric triglyceride, glyceryl stearate, glyceryl stearate SE, cetearyl alcohol, butyrospermum parkii (shea) butter, dimethicone, squalane, phenoxyethanol, caprylyl glycol, xanthan gum, citrus paradisi, citrus reticulata (tangerine) peel oil, orange terpenes, allantoin, sodium hydroxide, tetrasodium EDTA, chrysanthemum parthenium (feverfew) extract, camellia sinensis leaf extract, glycyrrhiza glabra (licorice) root extract, ceramide NP

Questions:

888-FAB-3063

MADE IN USA

FIRST AID BEAUTY LTD

NEWTON, MA 02458

WWW.FIRSTAIDBEAUTY.COM

PRINCIPAL DISPLAY PANEL - 396.8 g (14 oz)

First Aid Beauty

FAB

Ultra Repair® Cream

Intense Hydration

Skin Protectant Colloidal Oatmeal

Winter Citrus

Net Wt. 396.8 g (14 oz)